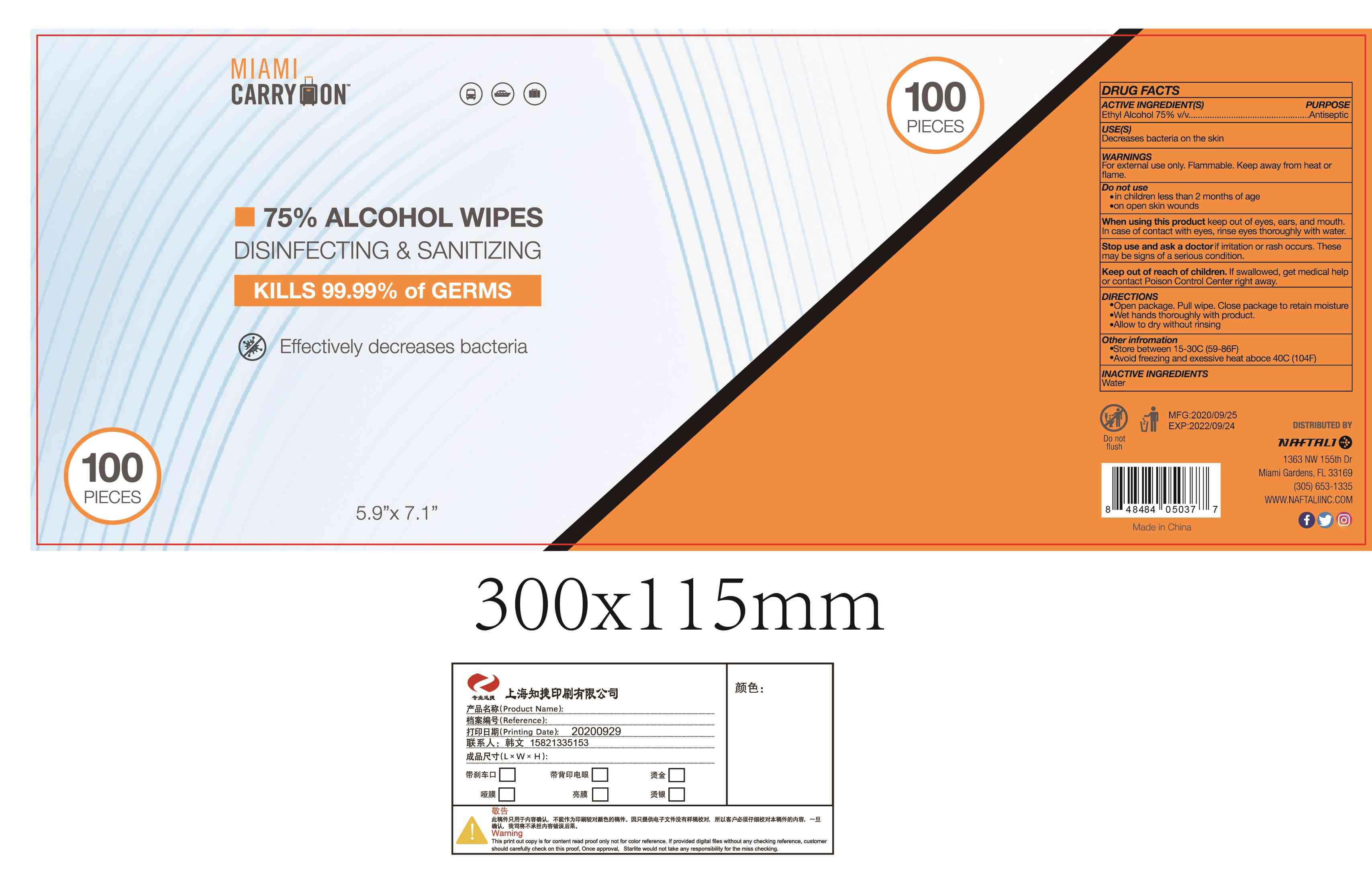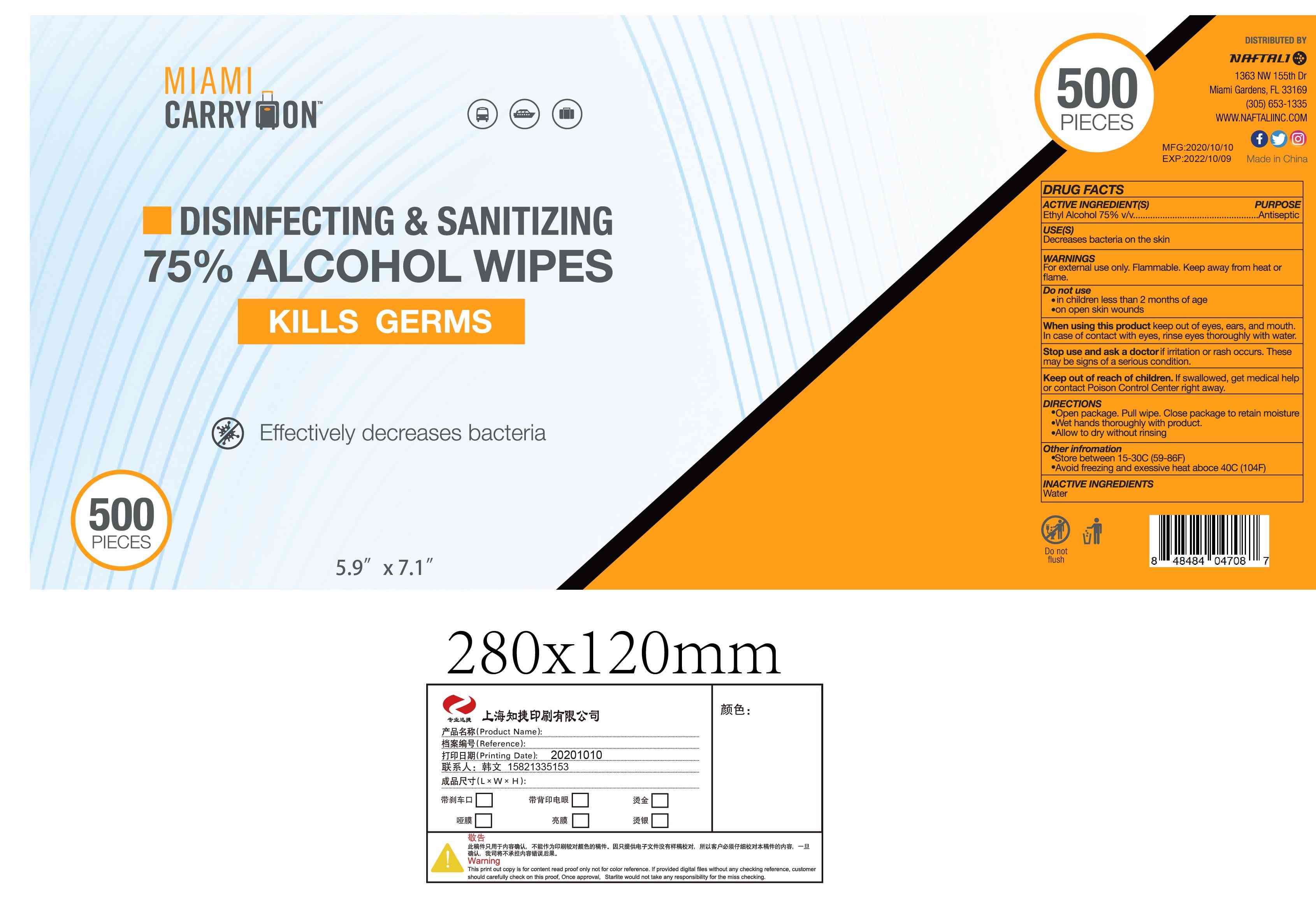 DRUG LABEL: ALCOHOL WIPES
NDC: 42003-207 | Form: CLOTH
Manufacturer: Zhejiang Jiayan Daily Commodity Co., Ltd
Category: otc | Type: HUMAN OTC DRUG LABEL
Date: 20220225

ACTIVE INGREDIENTS: ALCOHOL 75 mL/100 1
INACTIVE INGREDIENTS: WATER

42003-207
ALCOHOL WIPES

Active Ingredient(s)

Ethyl Alcohol 75% v/v

Purpose

Antiseptic

Use

Decreases bacteria on the skin

Warnings

For external use only. Flarnmable. Keep av-,ay from heat or flarne.

Do not use

in childr&n less than 2 months of age
on open skin wounds

When using this product keep out of eyes, ears, and mouth. In case of contact with eyes, rinse eyes thoroughly with water.

Stop use and ask a doctor if irritation or rash occurs. These may be signs of a sefious condition.

KEEP OUT OF REACH OF CHILDREN

Keep out of reach o1 children. If swallowed, get medical help or contact Poison Control Center right away.

Directions

Open package. Pull wipe. Close package to retain moisture
Wet hands thoroughly with product.
Allow to dry without rinsing.

Other information

store between 15-30C (59-86F)
Avoid freezing and exessive heat aboce 40C (104F)

Inactive ingredients

Water